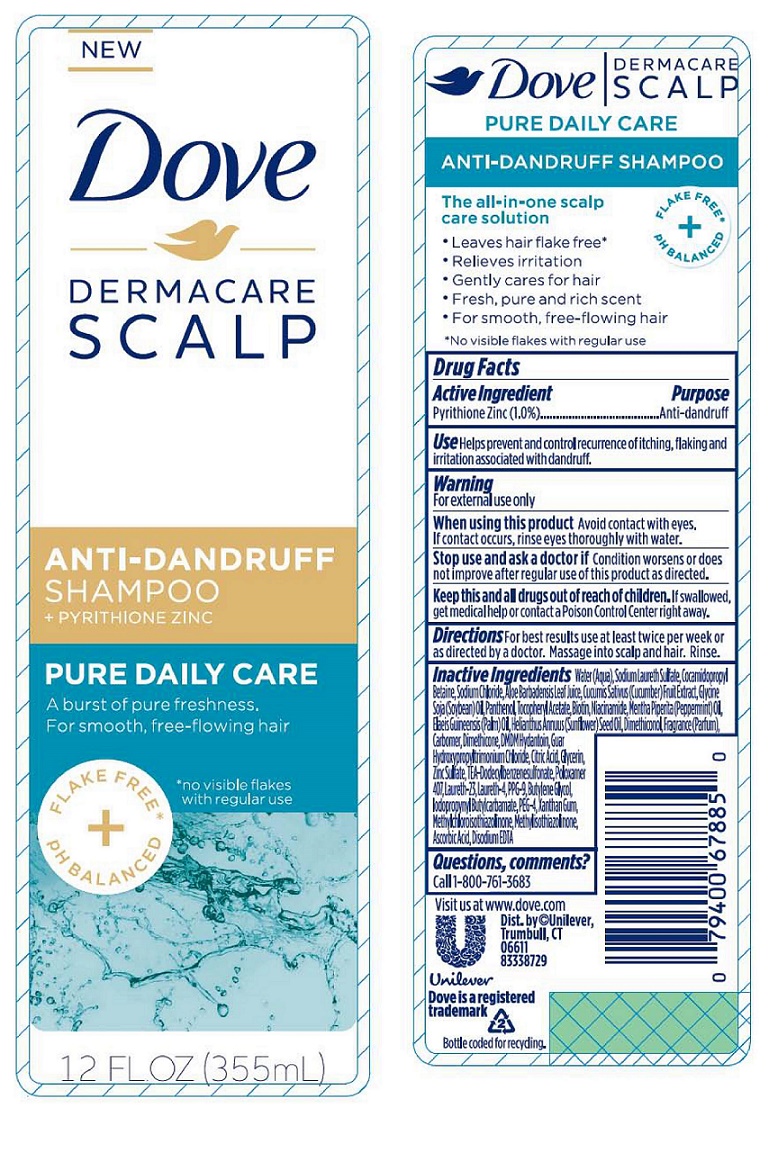 DRUG LABEL: Dove

NDC: 64942-1484 | Form: SHAMPOO
Manufacturer: Conopco, Inc. d/b/a Unilever
Category: otc | Type: HUMAN OTC DRUG LABEL
Date: 20221207

ACTIVE INGREDIENTS: PYRITHIONE ZINC 1 g/100 mL
INACTIVE INGREDIENTS: WATER; SODIUM LAURETH-3 SULFATE; COCAMIDOPROPYL BETAINE; SODIUM CHLORIDE; ALOE VERA LEAF; CUCUMBER; SOYBEAN OIL; PANTHENOL; .ALPHA.-TOCOPHEROL ACETATE, D-; BIOTIN; NIACINAMIDE; PEPPERMINT OIL; PALM OIL; SUNFLOWER OIL; DIMETHICONOL (40 CST); CARBOMER HOMOPOLYMER TYPE C (ALLYL PENTAERYTHRITOL CROSSLINKED); DIMETHICONE; DMDM HYDANTOIN; GUAR HYDROXYPROPYLTRIMONIUM CHLORIDE (1.7 SUBSTITUENTS PER SACCHARIDE); CITRIC ACID MONOHYDRATE; GLYCERIN; ZINC SULFATE, UNSPECIFIED FORM; TRIETHANOLAMINE DODECYLBENZENESULFONATE; POLOXAMER 407; LAURETH-23; LAURETH-4; PPG-9; BUTYLENE GLYCOL; IODOPROPYNYL BUTYLCARBAMATE; POLYETHYLENE GLYCOL 200; XANTHAN GUM; METHYLCHLOROISOTHIAZOLINONE; METHYLISOTHIAZOLINONE; ASCORBIC ACID; EDETATE DISODIUM

Dove Dermacare Scalp Pure Daily Care Anti-Dandruff Shampoo

Active Ingredient

Pyrithione Zinc (1.0%)

Purpose

Anti-dandruff

Use

Helps prevent and control recurrence of itching, flaking and irritation associated with dandruff.

Warning

For external use only

When using this product Avoid contact with eyes. If contact occurs, rinse eyes thoroughly with water.

Stop use and ask a doctor if condition worsens or does not improve after regular use of this product as directed.

KEEP OUT OF REACH OF CHILDREN

Keep this and all drugs out of reach of children. If swallowed, get medical help or contact a Poison Control Center right away.

Directions

For best results use at least twice per week or as directed by a doctor. Massage into scalp and hair. Rinse.

Inactive ingredients

Water, Sodium Laureth Sulfate, Cocamidopropyl Betaine, Sodium Chloride, Aloe Barbadensis Leaf Juice, Cucumis Sativus (Cucumber) Fruit Extract, Glycine Soja (Soybean) Oil, Panthenol, Tocopheryl Acetate, Biotin, Niacinamide, Mentha Piperita (Peppermint) Oil, Elaeis Guineensis (Palm) Oil, Helianthus Annuus (Sunflower) Seed Oil, Dimethiconol, Fragrance (Parfum), Carbomer, Dimethicone, DMDM Hydantoin, Guar Hydroxypropyltrimonium Chloride, Citric Acid, Glycerin, Zinc Sulfate, TEA-Dodecylbenzenesulfonate, Poloxamer 407, Laureth-23, Laureth-4, PPG-9, Butylene Glycol, Iodopropynyl Butylcarbamate, PEG-4, Xanthan Gum, Methylchloroisothiazolinone, Methylisothiazolinone, Ascorbic Acid, Disodium EDTA

Questions, comments?

Call 1-800-761-3683

PURE DAILY CARE

The all-in-one scalp care solution

- Leaves hair flake free*
- Relieves irritation
- Gently cares for hair
- Fresh, pure and rich scent
- For smooth, free-flowing hair

*No visible flakes with regular use